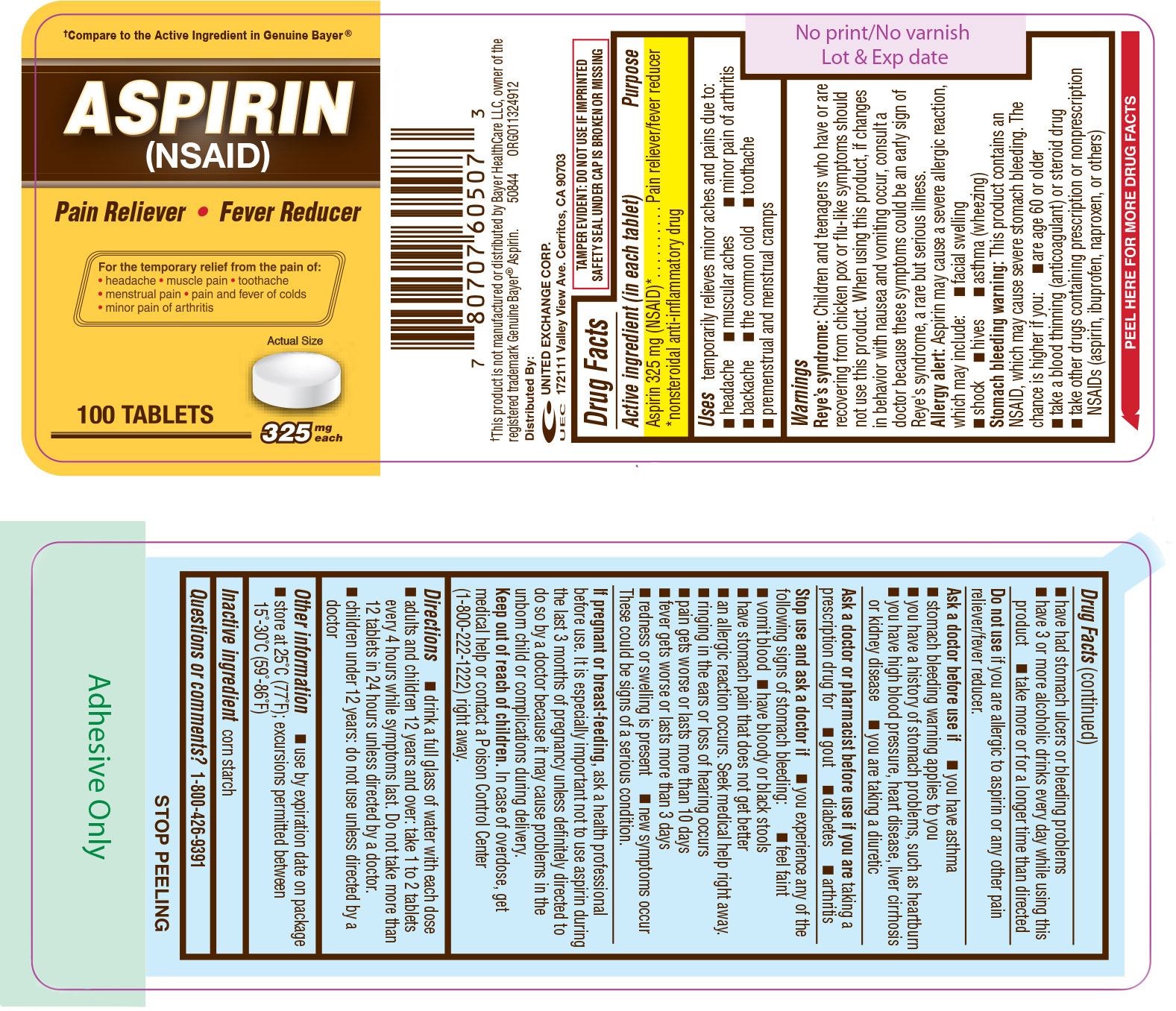 DRUG LABEL: Aspirin
NDC: 65923-507 | Form: TABLET
Manufacturer: United Exchange Corp.
Category: otc | Type: HUMAN OTC DRUG LABEL
Date: 20191206

ACTIVE INGREDIENTS: ASPIRIN 325 mg/1 1
INACTIVE INGREDIENTS: STARCH, CORN

Aspirin 100 Tablets 60507, 2019

Active ingredient (in each tablet) Purpose

Aspirin 325 mg (NSAID)*....................................Pain reliever/fever reducer

*nonsteroidal anti-inflammatory drug

Uses

temporarily relieves minor aches and pains due to:

- headache
- muscual aches
- minor pain of arthritis
- backache
- the common cold
- toothache
- premenstrual and menstrual cramps

Warnings

Reye's syndrome: Children and teenagers who have or are recovering from chicken pox or flu-like symptoms should not use this product. When using this product, if changes in behavior with nausea and vomiting occur, consult a doctor because these symptoms could be an early sign of Reye's syndrome, a rare but serious illness.

Allergy alert: Aspirin may cause a severe allergic reaction, which may include:

- facial swelling
- shock
- hives
- asthma (wheezing)

Stomach bleeding warning: This product contains an NSAID, which may cause severe stomach bleeding. The chance is higher if you:

- are age 60 or older
- take a blood thinning (anticoagulant) or steroid drug
- take other drugs containing prescription or nonprescription NSAIDs (aspirin, ibuprofen, naproxen, or others)
- have had stomach ulcers or bleeding problems
- have 3 or more alcoholic drinks every day while using this product
- take more or for a longer time than directed

Do not use if you are allergic to aspirin or any other pain reliever/fever reducer

Ask a doctor before use if

- you have asthma
- stomach bleeding warning applies to you
- you have a history of stomach problems, such as heartburn
- you have high blood pressure, heart disease, liver cirrhosis or kidney disease
- you are taking a diuretic

Ask a doctor or pharmacist before use if you are taking a prescription drug for

- gout
- diabetes
- arhiritis

Stop use and ask a doctor if

- you experience any of the following signs of stomach bleeding:
- feel faint
- vomit blood
- have bloddy or black stools
- have stomach pain that does not get better
- an allergic reaction occurs. Seek medical help right away.
- ringing in the ears or loss of hearing occurs
- pain gets worse or lasts more than 3 days
- redness or swelling is present
- new symptoms occur

These could be signs of a serious condition.

PREGNANCY OR BREAST FEEDING

If pregnant or breast-feeding, ask a health professional before use. It is especially important not to use aspirin during the last 3 months of pregnancy unless definitely directed to do so by a doctor because it may cause problems in the unborn child or complications during delivery.

Keep out of reach of children. In case of overdose, get medical help or contact a Poison Control Center (1-800-222-1222) right away.

Directions

- drink a full glass of water with each dose
- adults and children 12 years and over: take 1 to 2 tablets every 4 hours while symptoms last. Do not take more than 12 tablets in 24 hours unless directed by a doctor.
- children under 12 years: do not use unless directed by a doctor

Other information

- use by expiration date on package
- store at 25°C (77°F); excursions permitted between 15°-30°C (59°-86°F)

Inactive ingredient corn starch

DOSAGE AND ADMINISTRATION

Distributed by:

United Exchange Corp.

17211 Valley View Ave.

Cerritos, CA 90703

Made in USA